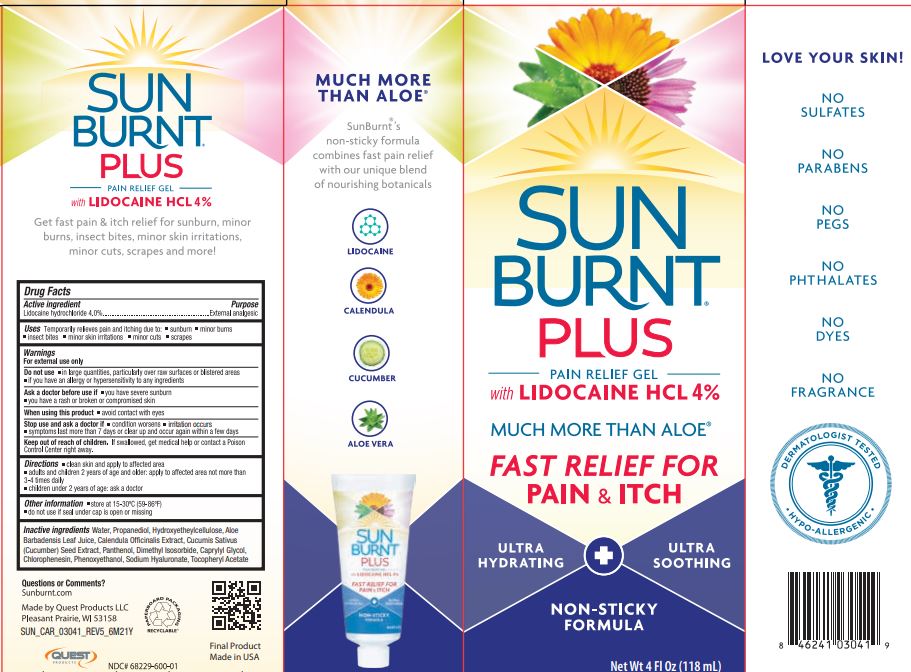 DRUG LABEL: SunBurnt PLUS
NDC: 68229-600 | Form: GEL
Manufacturer: Quest Products, LLC.
Category: otc | Type: HUMAN OTC DRUG LABEL
Date: 20260218

ACTIVE INGREDIENTS: LIDOCAINE HYDROCHLORIDE 4 g/100 mL
INACTIVE INGREDIENTS: PROPANEDIOL; ALOE VERA LEAF; DIMETHYL ISOSORBIDE; HYDROXYETHYL CELLULOSE (5500 MPA.S AT 2%); PHENOXYETHANOL; CHLORPHENESIN; .ALPHA.-TOCOPHEROL ACETATE; WATER; CAPRYLYL GLYCOL; CALENDULA OFFICINALIS FLOWER; PANTHENOL; CUCUMBER SEED; HYALURONATE SODIUM

SunBurnt® PLUS

Drug Facts

Active Ingredient

Lidocaine Hydrochloride 4.0%

Purpose

External analgesic

Uses

Temporarily relieves pain and itching due to:

- sunburn
- minor burns
- insect bites
- minor skin irritations
- minor cuts
- scrapes

Warnings

For external use only

Do not use

- in large quantities, particularly over raw surfaces or blistered areas
- if you have an allergy or hypersensitivity to any ingredients

Ask a doctor before use if

- you have severe sunburn
- you have a rash or broken or compromised skin

When using this product

- Avoid contact with eyes

Stop use and ask a doctor

- condition worsens
- symptoms last more than 7 days or clear up and occur again within a few days

Keep out of reach of children. If swallowed, get medical help or contact a Poison Control Center right away.

Directions

- clean skin and apply to affected area
- adults and children 2 years of age and older: apply to affected area not more than 3-4 times daily
- children under 2 years of age: ask a doctor

Other Information

- store at 15-30°C (59-86°F)
- do not use if seal under cap is open or missing

Inactive Ingredients

Water, Propanediol,Hydroxyethylcellulose, Aloe Barbadensis Leaf Juice, Calunda Officinalis Extract, Cucumis Sativus (Cucumber) Seed Extract, Panthenol, Dimethyl Isosorbide, Caprylyl Glycol, Chlorophenesin, Phenoxyethanol, Sodium Hyaluronate, Tocopheryl Acetate

Questions or Comments?

Sunburnt.com